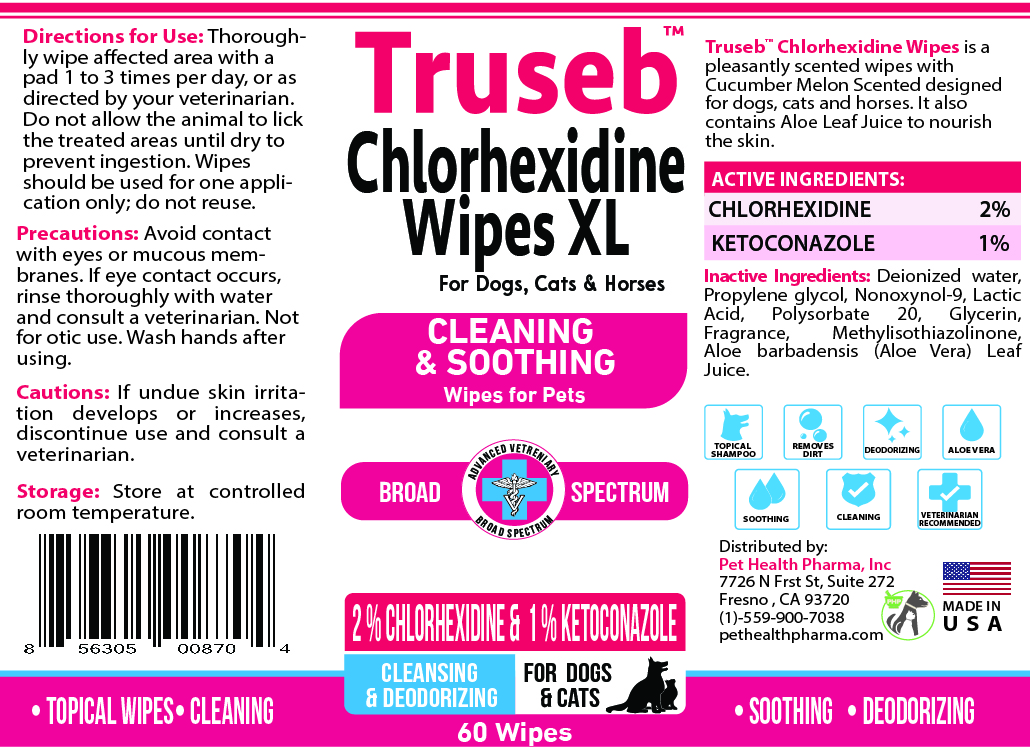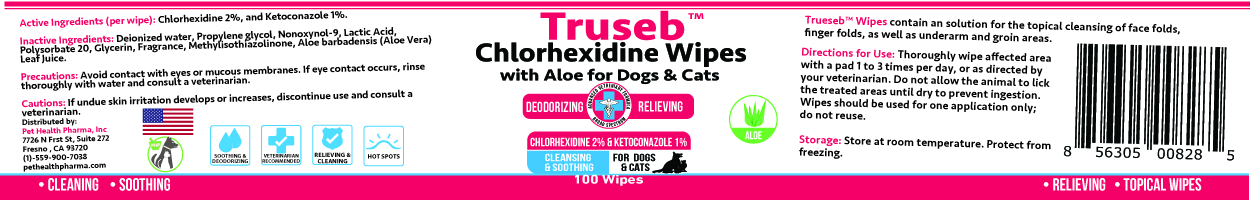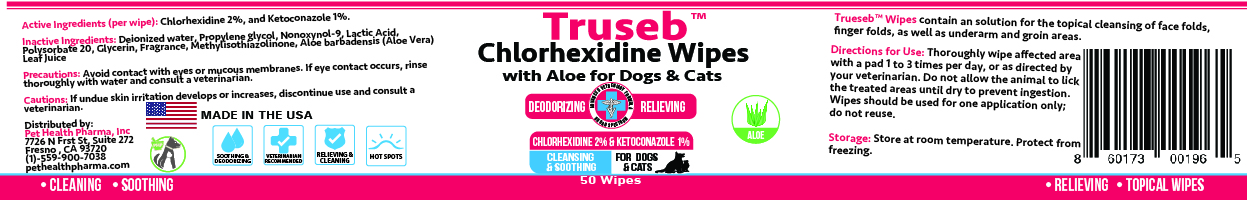 DRUG LABEL: TRUSEB ANTISEPTIC, ANTI-BACTERIAL AND ANTI-FUNGAL WIPES WITH ALOE FOR DOGS, CATS AND HORSES
NDC: 86176-104 | Form: CLOTH
Manufacturer: Pet Health Pharma, LLC
Category: animal | Type: OTC ANIMAL DRUG LABEL
Date: 20250212

ACTIVE INGREDIENTS: Chlorhexidine Gluconate 20 mg/1 1; KETOCONAZOLE 10 mg/1 1
INACTIVE INGREDIENTS: WATER; PROPYLENE GLYCOL; NONOXYNOL-9; LACTIC ACID, UNSPECIFIED FORM; POLYSORBATE 20; GLYCERIN; ALOE VERA LEAF; METHYLISOTHIAZOLINONE

TRUSEB CHLORHEXIDINE WITH ALOE FOR DOGS, CATS AND HORSES

Active Ingredients:

Chlorhexidine Gluconate 2% and Ketoconazole 1%

INDICATIONS & USAGE:

Trueseb™ Wipes contain an solution for the topical cleansing of face folds, finger folds, as well as underarm and groin areas.

INACTIVE INGREDIENT:

Water, Propylene Glycol, Nonoxynol-9, Lactic Acid, Polysorbate 20, Glycerin, Fragrance, Methylisothiazolinone, Aloe Barbadensis (Aloe) Leaf Juice.

DOSAGE & ADMINISTRATION:

Thoroughly wipe affected area with a pad 1 to 3 times per day, or as directed by your veterinarian. Do not allow the animal to lick the treated areas until dry to prevent ingestion. Wipes should be used for one application only; do not reuse.

PRECAUTIONS:

Avoid contact with eyes or mucous membranes. If eye contact occurs, rinse thoroughly with water and consult a veterinarian.

STORAGE AND HANDLING:

Store at controlled room temperature.

CAUTION:

If undue skin irritation develops or increases, discontinue use and consult a veterinarian.

SPL UNCLASSIFIED SECTION:

Chlorhexidine Wipes
with Aloe for Dogs & Cats
SOOTHING & DEODORIZING
VETERINARIAN RECOMMENDED
RELIEVING & CLEANING
HOT SPOTS
Aloe
Deodorizing Relieving
Soothing Aloe Vera
• Cleaning • Soothing
• Relieving • Topical wipes
MADE IN THE USA

Distributed by:
Pet Health Pharma, Inc
7726 N Frst St, Suite 272
Fresno , CA 93720
(1)-559-900-7038
pethealthpharma.com

Packaging

Add image transcription here...

Add image transcription here...

Add image transcription here...